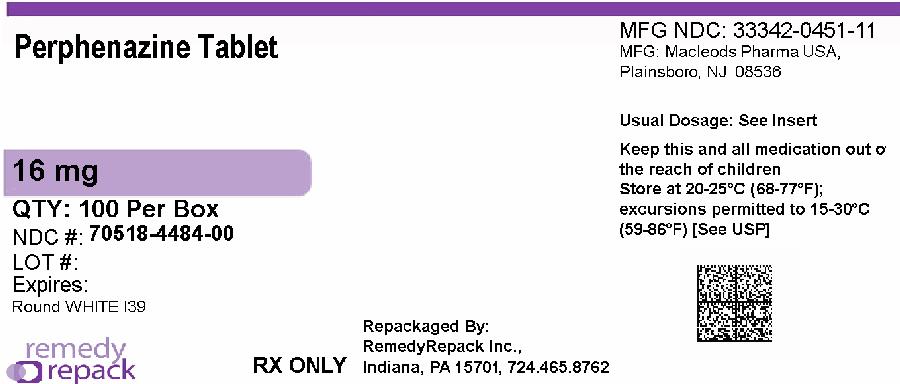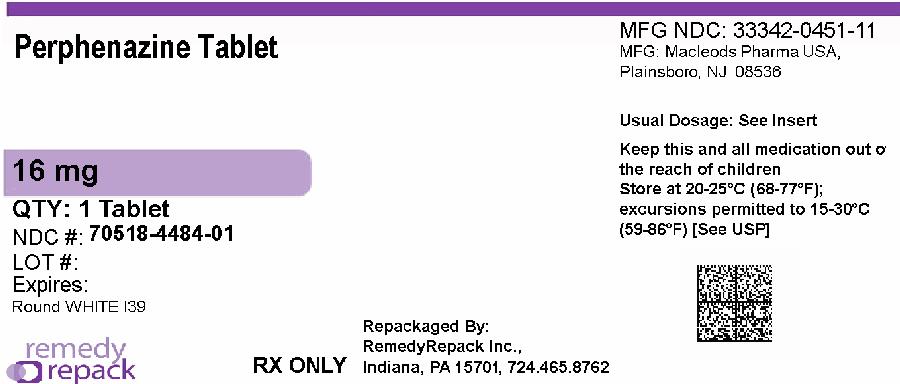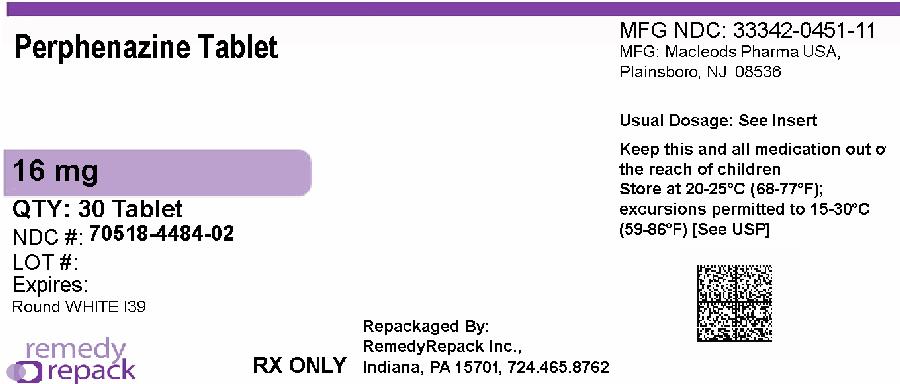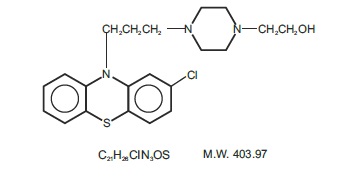 DRUG LABEL: Perphenazine
NDC: 70518-4484 | Form: TABLET
Manufacturer: REMEDYREPACK INC.
Category: prescription | Type: HUMAN PRESCRIPTION DRUG LABEL
Date: 20260120

ACTIVE INGREDIENTS: PERPHENAZINE 16 mg/1 1
INACTIVE INGREDIENTS: CELLULOSE, MICROCRYSTALLINE; LACTOSE MONOHYDRATE; SODIUM STARCH GLYCOLATE TYPE A POTATO; HYDROXYPROPYL CELLULOSE; MAGNESIUM STEARATE; POLYETHYLENE GLYCOL 400; POLYSORBATE 80; TITANIUM DIOXIDE; HYPROMELLOSES

Perphenazine Tablets, USP

WARNING

Increased Mortality in Elderly Patients with Dementia-Related Psychosis

Elderly patients with dementia-related psychosis treated with antipsychotic drugs are at an increased risk of death. Analyses of seventeen placebo-controlled trials (modal duration of 10 weeks), largely in patients taking atypical antipsychotic drugs, revealed a risk of death in drug-treated patients of between 1.6 to 1.7 times the risk of death in placebo-treated patients. Over the course of a typical 10-week controlled trial, the rate of death in drug-treated patients was about 4.5%, compared to a rate of about 2.6% in the placebo group. Although the causes of death were varied, most of the deaths appeared to be either cardiovascular (e.g., heart failure, sudden death) or infectious (e.g., pneumonia) in nature. Observational studies suggest that, similar to atypical antipsychotic drugs, treatment with conventional antipsychotic drugs may increase mortality. The extent to which the findings of increased mortality in observational studies may be attributed to the antipsychotic drug as opposed to some characteristic(s) of the patients is not clear. Perphenazine is not approved for the treatment of patients with dementia-related psychosis (see WARNINGS).

DESCRIPTION

Perphenazine (4-[3-(2-chlorophenothiazin-10-yl)propyl]-1-piperazineethanol), a piperazinyl phenothiazine, having the chemical formula, C21H26CIN3OS. It is available as oral tablets containing 2 mg, 4 mg, 8 mg, and 16 mg of perphenazine.
Inactive ingredients: microcrystalline cellulose, lactose (monohydrate), hypromellose, sodium starch glycolate, hydroxypropyl cellulose and magnesium stearate. The composition of coating material for perphenazine tablets, USP 2 mg, 4 mg, 8 mg, and 16 mg: hypromellose, polyethylene glycol, polysorbate 80, and titanium dioxide. Its structural formula is:

ACTIONS

Perphenazine has actions at all levels of the central nervous system, particularly the hypothalamus. However, the site and mechanism of action of therapeutic effect are not known.

CLINICAL PHARMACOLOGY

Pharmacokinetics
Following oral administration of perphenazine tablets, mean peak plasma perphenazine concentrations were observed between 1 to 3 hours. The plasma elimination half-life of perphenazine was independent of dose and ranged between 9 and 12 hours. In a study in which normal volunteers (n=12) received perphenazine 4 mg q8h for 5 days, steady-state concentrations of perphenazine were reached within 72 hours. Mean (%CV) Cmaxand Cminvalues for perphenazine and 7-hydroxyperphenazine at steady-state are listed below:

Parameter | Perphenazine | 7-Hydroxyperphenazine
Cmax(pg/mL) | 984 (43) | 509 (25)
Cmin(pg/mL) | 442 (76) | 350 (56)

Peak 7-hydroxyperphenazine concentrations were observed between 2 to 4 hours with a terminal phase half-life ranging between 9.9 to 18.8 hours. Perphenazine is extensively metabolized in the liver to a number of metabolites by sulfoxidation, hydroxylation, dealkylation, and glucuronidation. The pharmacokinetics of perphenazine covary with the hydroxylation of debrisoquine which is mediated by cytochrome P450 2D6 (CYP 2D6) and thus is subject to genetic polymorphism – i.e., 7% to 10% of Caucasians and a low percentage of Asians have little or no activity and are called “poor metabolizers.” Poor metabolizers of CYP 2D6 will metabolize perphenazine more slowly and will experience higher concentrations compared with normal or “extensive” metabolizers.

INDICATIONS & USAGE

Perphenazine is indicated for use in the treatment of schizophrenia and for the control of severe nausea and vomiting in adults.
Perphenazine has not been shown effective for the management of behavioral complications in patients with mental retardation.

CONTRAINDICATIONS

Perphenazine products are contraindicated in comatose or greatly obtunded patients and in patients receiving large doses of central nervous system depressants (barbiturates, alcohol, narcotics, analgesics, or antihistamines); in the presence of existing blood dyscrasias, bone marrow depression, or liver damage; and in patients who have shown hypersensitivity to perphenazine products, their components, or related compounds.
Perphenazine products are also contraindicated in patients with suspected or established subcortical brain damage, with or without hypothalamic damage, since a hyperthermic reaction with temperatures in excess of 104°F may occur in such patients, sometimes not until 14 to 16 hours after drug administration. Total body ice-packing is recommended for such a reaction; antipyretics may also be useful.

WARNINGS

Increased Mortality in Elderly Patients with Dementia-Related Psychosis
Elderly patients with dementia-related psychosis treated with antipsychotic drugs are at an increased risk of death. Perphenazine is not approved for the treatment of patients with dementia-related psychosis (see BOXED WARNING).

Tardive dyskinesia, a syndrome consisting of potentially irreversible, involuntary, dyskinetic movements, may develop in patients treated with antipsychotic drugs. Older patients are at increased risk for development of tardive dyskinesia. Although the prevalence of the syndrome appears to be highest among the elderly, especially elderly women, it is impossible to rely upon prevalence estimates to predict, at the inception of antipsychotic treatment, which patients are likely to develop the syndrome. Whether antipsychotic drug products differ in their potential to cause tardive dyskinesia is unknown.
Both the risk of developing the syndrome and the likelihood that it will become irreversible are believed to increase as the duration of treatment and the total cumulative dose of antipsychotic drugs administered to the patient increase. However, the syndrome can develop, although much less commonly, after relatively brief treatment periods at low doses.
There is no known treatment for established cases of tardive dyskinesia, although the syndrome may remit, partially or completely, if antipsychotic treatment is withdrawn. Antipsychotic treatment itself, however, may suppress (or partially suppress) the signs and symptoms of the syndrome, and thereby may possibly mask the underlying disease process. The effect that symptomatic suppression has upon the long-term course of the syndrome is unknown.
Given these considerations, especially in the elderly, antipsychotics should be prescribed in a manner that is most likely to minimize the occurrence of tardive dyskinesia. Chronic antipsychotic treatment should generally be reserved for patients who suffer from a chronic illness that 1) is known to respond to antipsychotic drugs, and 2) for whom alternative, equally effective, but potentially less harmful treatments are not available or appropriate. In patients who do require chronic treatment, the smallest dose and the shortest duration of treatment producing a satisfactory clinical response should be sought. The need for continued treatment should be reassessed periodically.
If signs and symptoms of tardive dyskinesia appear in a patient on antipsychotics, drug discontinuation should be considered. However, some patients may require treatment despite the presence of the syndrome.
(For further information about the description of tardive dyskinesia and its clinical detection, please refer to Information for Patientsand
ADVERSE REACTIONS.)
Neuroleptic Malignant Syndrome (NMS)
A potentially fatal symptom complex, sometimes referred to as Neuroleptic Malignant Syndrome (NMS), has been reported in association with antipsychotic drugs. Clinical manifestations of NMS are hyperpyrexia, muscle rigidity, altered mental status and evidence of autonomic instability (irregular pulse or blood pressure, tachycardia, diaphoresis, and cardiac dysrhythmias).
The diagnostic evaluation of patients with this syndrome is complicated. In arriving at a diagnosis, it is important to identify cases where the clinical presentation includes both serious medical illness (e.g., pneumonia, systemic infection, etc.) and untreated or inadequately treated extrapyramidal signs and symptoms (EPS). Other important considerations in the differential diagnosis include central anticholinergic toxicity, heat stroke, drug fever and primary central nervous system (CNS) pathology.
The management of NMS should include 1) immediate discontinuation of antipsychotic drugs and other drugs not essential to concurrent therapy, 2) intensive symptomatic treatment and medical monitoring, and 3) treatment of any concomitant serious medical problems for which specific treatments are available. There is no general agreement about specific pharmacological treatment regimens for uncomplicated NMS.
If a patient requires antipsychotic drug treatment after recovery from NMS, the reintroduction of drug therapy should be carefully considered. The patient should be carefully monitored, since recurrences of NMS have been reported.
If hypotension develops, epinephrine should not be administered since its action is blocked and partially reversed by perphenazine. If a vasopressor is needed, norepinephrine may be used. Severe, acute hypotension has occurred with the use of phenothiazines and is particularly likely to occur in patients with mitral insufficiency or pheochromocytoma. Rebound hypertension may occur in pheochromocytoma patients.
Perphenazine products can lower the convulsive threshold in susceptible individuals; they should be used with caution in alcohol withdrawal and in patients with convulsive disorders. If the patient is being treated with an anticonvulsant agent, increased dosage of that agent may be required when perphenazine products are used concomitantly.
Perphenazine products should be used with caution in patients with psychic depression.
Perphenazine may impair the mental and/or physical abilities required for the performance of hazardous tasks such as driving a car or operating machinery; therefore, the patient should be warned accordingly.
Perphenazine products are not recommended for pediatric patients under 12 years of age.
Falls
Perphenazine tablets may cause somnolence, postural hypotension, motor and sensory instability, which may lead to falls and, consequently, fractures or other injuries. For patients with diseases, conditions, or medications that could exacerbate these effects, complete fall risk assessments when initiating antipsychotic treatment and recurrently for patients on long-term antipsychotic therapy.
Usage in Pregnancy
Non-teratogenic Effects
Neonates exposed to antipsychotic drugs, during the third trimester of pregnancy are at risk for extrapyramidal and/or withdrawal symptoms following delivery. There have been reports of agitation, hypertonia, hypotonia, tremor, somnolence, respiratory distress and feeding disorder in these neonates. These complications have varied in severity; while in some cases symptoms have been self-limited, in other cases neonates have required intensive care unit support and prolonged hospitalization.
Perphenazine should be used during pregnancy only if the potential benefit justifies the potential risk to the fetus.
Safe use of perphenazine during pregnancy and lactation has not been established; therefore, in administering the drug to pregnant patients, nursing mothers, or women who may become pregnant, the possible benefits must be weighed against the possible hazards to mother and child.

PRECAUTIONS

Leukopenia, Neutropenia and Agranulocytosis
In clinical trial and postmarketing experience, events of leukopenia/neutropenia and agranulocytosis have been reported temporally related to antipsychotic agents.
Possible risk factors for leukopenia/neutropenia include preexisting low white blood cell count (WBC) and history of drug induced leukopenia/neutropenia. Patients with a preexisting low WBC or a history of drug induced leukopenia/neutropenia should have their complete blood count (CBC) monitored frequently during the first few months of therapy and should discontinue perphenazine tablets USP at the first sign of a decline in WBC in the absence of other causative factors.
Patients with neutropenia should be carefully monitored for fever or other symptoms or signs of infection and treated promptly if such symptoms or signs occur. Patients with severe neutropenia (absolute neutrophil count <1000/mm^3) should discontinue perphenazine tablets USP and have their WBC followed until recovery.
The possibility of suicide in depressed patients remains during treatment and until significant remission occurs. This type of patient should not have access to large quantities of this drug.
As with all phenothiazine compounds, perphenazine should not be used indiscriminately. Caution should be observed in giving it to patients who have previously exhibited severe adverse reactions to other phenothiazines. Some of the untoward actions of perphenazine tend to appear more frequently when high doses are used. However, as with other phenothiazine compounds, patients receiving perphenazine products in any dosage should be kept under close supervision.
Antipsychotic drugs elevate prolactin levels; the elevation persists during chronic administration. Tissue culture experiments indicate that approximately one-third of human breast cancers are prolactin dependent in vitro,a factor of potential importance if the prescription of these drugs is contemplated in a patient with a previously detected breast cancer. Although disturbances such as galactorrhea, amenorrhea, gynecomastia, and impotence have been reported, the clinical significance of elevated serum prolactin levels is unknown for most patients. An increase in mammary neoplasms has been found in rodents after chronic administration of antipsychotic drugs. Some epidemiologic studies have indicated a potential association between chronic administration of prolactinincreasing antipsychotics and breast cancer.
The antiemetic effect of perphenazine may obscure signs of toxicity due to overdosage of other drugs, or render more difficult the diagnosis of disorders such as brain tumors or intestinal obstruction.
A significant, not otherwise explained, rise in body temperature may suggest individual intolerance to perphenazine, in which case it should be discontinued.
Patients on large doses of a phenothiazine drug who are undergoing surgery should be watched carefully for possible hypotensive phenomena. Moreover, reduced amounts of anesthetics or central nervous system depressants may be necessary.
Since phenothiazines and central nervous system depressants (opiates, analgesics, antihistamines, barbiturates) can potentiate each other, less than the usual dosage of the added drug is recommended and caution is advised when they are administered concomitantly.
Use with caution in patients who are receiving atropine or related drugs because of additive anticholinergic effects and also in patients who will be exposed to extreme heat or phosphorus insecticides.
The use of alcohol should be avoided, since additive effects and hypotension may occur. Patients should be cautioned that their response to alcohol may be increased while they are being treated with perphenazine products. The risk of suicide and the danger of overdose may be increased in patients who use alcohol excessively due to its potentiation of the drug’s effect.
Blood counts and hepatic and renal functions should be checked periodically. The appearance of signs of blood dyscrasias requires the discontinuance of the drug and institution of appropriate therapy. If abnormalities in hepatic tests occur, phenothiazine treatment should be discontinued. Renal function in patients on long-term therapy should be monitored; if blood urea nitrogen (BUN) becomes abnormal, treatment with the drug should be discontinued.
The use of phenothiazine derivatives in patients with diminished renal function should be undertaken with caution.
Use with caution in patients suffering from respiratory impairment due to acute pulmonary infections, or in chronic respiratory disorders such as severe asthma or emphysema.
In general, phenothiazines, including perphenazine, do not produce psychic dependence. Gastritis, nausea and vomiting, dizziness, and tremulousness have been reported following abrupt cessation of high-dose therapy. Reports suggest that these symptoms can be reduced by continuing concomitant antiparkinson agents for several weeks after the phenothiazine is withdrawn.
The possibility of liver damage, corneal and lenticular deposits, and irreversible dyskinesias should be kept in mind when patients are on long-term therapy.
Because photosensitivity has been reported, undue exposure to the sun should be avoided during phenothiazine treatment.

Drug Interactions

Metabolism of a number of medications, including antipsychotics, antidepressants, β-blockers, and antiarrhythmics, occurs through the cytochrome P450 2D6 isoenzyme (debrisoquine hydroxylase). Approximately 10% of the Caucasian population has reduced activity of this enzyme, so-called “poor” metabolizers. Among other populations the prevalence is not known. Poor metabolizers demonstrate higher plasma concentrations of antipsychotic drugs at usual doses, which may correlate with emergence of side effects. In one study of 45 elderly patients suffering from dementia treated with perphenazine, the 5 patients who were prospectively identified as poor P450 2D6 metabolizers had reported significantly greater side effects during the first 10 days of treatment than the 40 extensive metabolizers, following which the groups tended to converge. Prospective phenotyping of elderly patients prior to antipsychotic treatment may identify those at risk for adverse events.
The concomitant administration of other drugs that inhibit the activity of P450 2D6 may acutely increase plasma concentrations of antipsychotics. Among these are tricyclic antidepressants and selective serotonin reuptake inhibitors, e.g., fluoxetine, sertraline and paroxetine. When prescribing these drugs to patients already receiving antipsychotic therapy, close monitoring is essential and dose reduction may become necessary to avoid toxicity. Lower doses than usually prescribed for either the antipsychotic or the other drug may be required.
Information for Patients
This information is intended to aid in the safe and effective use of this medication. It is not a disclosure of all possible adverse or intended effects.
Given the likelihood that a substantial proportion of patients exposed chronically to antipsychotics will develop tardive dyskinesia, it is advised that all patients in whom chronic use is contemplated be given, if possible, full information about this risk. The decision to inform patients and/or their guardians must obviously take into account the clinical circumstances and the competency of the patient to understand the information provided.

Geriatric Use

Clinical studies of perphenazine products did not include sufficient numbers of subjects aged 65 and over to determine whether elderly subjects respond differently from younger subjects. Other reported clinical experience has not identified differences in responses between the elderly and younger patients. In general, dose selection for an elderly patient should be cautious, usually starting at the low end of the dosing range, reflecting the greater frequency of decreased hepatic function, concomitant disease or other drug therapy.
Geriatric patients are particularly sensitive to the side effects of antipsychotics, including perphenazine. These side effects include extrapyramidal symptoms (tardive dyskinesia, antipsychotic-induced parkinsonism, akathisia), anticholinergic effects, sedation and orthostatic hypotension (See WARNINGS). Elderly patients taking psychotropic drugs may be at increased risk for falling and consequent hip fractures. Elderly patients should be started on lower doses and observed closely.

ADVERSE REACTIONS

Not all of the following adverse reactions have been reported with this specific drug; however, pharmacological similarities among various phenothiazine derivatives require that each be considered. With the piperazine group (of which perphenazine is an example), the extrapyramidal symptoms are more common, and others (e.g., sedative effects, jaundice, and blood dyscrasias) are less frequently seen.
CNS Effects
Extrapyramidal Reactions
Opisthotonus, trismus, torticollis, retrocollis, aching and numbness of the limbs, motor restlessness, oculogyric crisis, hyperreflexia, dystonia, including protrusion, discoloration, aching and rounding of the tongue, tonic spasm of the masticatory muscles, tight feeling in the throat, slurred speech, dysphagia, akathisia, dyskinesia, parkinsonism, and ataxia. Their incidence and severity usually increase with an increase in dosage, but there is considerable individual variation in the tendency to develop such symptoms. Extrapyramidal symptoms can usually be controlled by the concomitant use of effective antiparkinsonian drugs, such as benztropine mesylate, and/or by reduction in dosage. In some instances, however, these extrapyramidal reactions may persist after discontinuation of treatment with perphenazine.
Dystonia
Class effect:Symptoms of dystonia, prolonged abnormal contractions of muscle groups, may occur in susceptible individuals during the first few days of treatment. Dystonic symptoms include: spasm of the neck muscles, sometimes progressing to tightness of the throat, swallowing difficulty, difficulty breathing, and/or protrusion of the tongue. While these symptoms can occur at low doses, they occur more frequently and with greater severity with high potency and at higher doses of first generation antipsychotic drugs. An elevated risk of acute dystonia is observed in males and younger age groups.
Persistent Tardive Dyskinesia
As with all antipsychotic agents, tardive dyskinesia may appear in some patients on long-term therapy or may appear after drug therapy has been discontinued. Although the risk appears to be greater in elderly patients on high-dose therapy, especially females, it may occur in either sex and in children. The symptoms are persistent and in some patients appear to be irreversible. The syndrome is characterized by rhythmical, involuntary movements of the tongue, face, mouth or jaw (e.g., protrusion of tongue, puffing of cheeks, puckering of mouth, chewing movements). Sometimes these may be accompanied by involuntary movements of the extremities. There is no known effective treatment for tardive dyskinesia; antiparkinsonism agents usually do not alleviate the symptoms of this syndrome. It is suggested that all antipsychotic agents be discontinued if these symptoms appear. Should it be necessary to reinstitute treatment, or increase the dosage of the agent, or switch to a different antipsychotic agent, the syndrome may be masked. It has been reported that fine, vermicular movements of the tongue may be an early sign of the syndrome, and if the medication is stopped at that time the syndrome may not develop.
Other CNS Effects
Include cerebral edema; abnormality of cerebrospinal fluid proteins; convulsive seizures, particularly in patients with EEG abnormalities or a history of such disorders; and headaches.
Neuroleptic malignant syndrome has been reported in patients treated with antipsychotic drugs (see WARNINGS).
Drowsiness may occur, particularly during the first or second week, after which it generally disappears. If troublesome, lower the dosage. Hypnotic effects appear to be minimal, especially in patients who are permitted to remain active.
Adverse behavioral effects include paradoxical exacerbation of psychotic symptoms, catatonic-like states, paranoid reactions, lethargy, paradoxical excitement, restlessness, hyperactivity, nocturnal confusion, bizarre dreams, and insomnia.
Hyperreflexia has been reported in the newborn when a phenothiazine was used during pregnancy.
Autonomic Effects
Dry mouth or salivation, nausea, vomiting, diarrhea, anorexia, constipation, obstipation, fecal impaction, urinary retention, frequency or incontinence, bladder paralysis, polyuria, nasal congestion, pallor, myosis, mydriasis, blurred vision, glaucoma, perspiration, hypertension, hypotension, and change in pulse rate occasionally may occur. Significant autonomic effects have been infrequent in patients receiving less than 24 mg perphenazine daily. Adynamic ileus occasionally occurs with phenothiazine therapy, and if severe, can result in complications and death. It is of particular concern in psychiatric patients, who may fail to seek treatment of the condition.
Allergic Effects
Urticaria, erythema, eczema, exfoliative dermatitis, pruritus, photosensitivity, asthma, fever, anaphylactoid reactions, laryngeal edema, and angioneurotic edema; contact dermatitis in nursing personnel administering the drug; and in extremely rare instances, individual idiosyncrasy or hypersensitivity to phenothiazines has resulted in cerebral edema, circulatory collapse, and death.
Endocrine Effects
Lactation, galactorrhea, moderate breast enlargement in females and gynecomastia in males on large doses, disturbances in the menstrual cycle, amenorrhea, changes in libido, inhibition of ejaculation, syndrome of inappropriate ADH (antidiuretic hormone) secretion, false positive pregnancy tests, hyperglycemia, hypoglycemia, glycosuria.

Cardiovascular Effects
Postural hypotension, tachycardia (especially with sudden marked increase in dosage), bradycardia, cardiac arrest, faintness, and dizziness. Occasionally the hypotensive effect may produce a shock-like condition. ECG changes, nonspecific (quinidine-like effect) usually reversible, have been observed in some patients receiving phenothiazine antipsychotics.
Sudden death has occasionally been reported in patients who have received phenothiazines. In some cases, the death was apparently due to cardiac arrest; in others, the cause appeared to be asphyxia due to failure of the cough reflex. In some patients, the cause could not be determined nor could it be established that the death was due to the phenothiazine.
Hematological Effects
Agranulocytosis, eosinophilia, leukopenia, hemolytic anemia, thrombocytopenic purpura, and pancytopenia. Most cases of agranulocytosis have occurred between the fourth and tenth weeks of therapy. Patients should be watched closely, especially during that period, for the sudden appearance of sore throat or signs of infection. If white blood cell and differential cell counts show significant cellular depression, discontinue the drug and start appropriate therapy. However, a slightly lowered white count is not in itself an indication to discontinue the drug.
Other Effects
Special considerations in long-term therapy include pigmentation of the skin, occurring chiefly in the exposed areas; ocular changes consisting of deposition of fine particulate matter in the cornea and lens, progressing in more severe cases to star-shaped lenticular opacities; epithelial keratopathies; and pigmentary retinopathy. Also noted: peripheral edema, reversed epinephrine effect, increase in PBI not attributable to an increase in thyroxine, parotid swelling (rare), hyperpyrexia, systemic lupus erythematosus-like syndrome, increases in appetite and weight, polyphagia, photophobia, and muscle weakness.
Liver damage (biliary stasis) may occur. Jaundice may occur, usually between the second and fourth weeks of treatment, and is regarded as a hypersensitivity reaction. Incidence is low. The clinical picture resembles infectious hepatitis but with laboratory features of obstructive jaundice. It is usually reversible; however, chronic jaundice has been reported.

To report SUSPECTED ADVERSE REACTIONS, contact Macleods Pharma USA, Inc. at 1-888-943-3210 or 1-855-926-3384 or FDA at 1-800-FDA-1088 or www.fda.gov/medwatch.

DOSAGE & ADMINISTRATION

Dosage must be individualized and adjusted according to the severity of the condition and the response obtained. As with all potent drugs, the best dose is the lowest dose that will produce the desired clinical effect. Since extrapyramidal symptoms increase in frequency and severity with increased dosage, it is important to employ the lowest effective dose. These symptoms have disappeared upon reduction of dosage, withdrawal of the drug, or administration of an antiparkinsonian agent.
Prolonged administration of doses exceeding 24 mg daily should be reserved for hospitalized patients or patients under continued observation for early detection and management of adverse reactions. An antiparkinsonian agent, such as trihexyphenidyl hydrochloride or benztropine mesylate, is valuable in controlling drug-induced extrapyramidal symptoms.
Suggested dosages for various conditions follow:
Moderately disturbed nonhospitalized patients with schizophrenia
4 to 8 mg t.i.d. initially; reduce as soon as possible to minimum effective dosage.
Hospitalized patients with schizophrenia
8 to 16 mg b.i.d. to q.i.d.; avoid dosages in excess of 64 mg daily.
Severe nausea and vomiting in adults
8 to 16 mg daily in divided doses; 24 mg occasionally may be necessary; early dosage reduction is desirable.
Elderly Patients
With increasing age, plasma concentrations of perphenazine per daily ingested dose increase. Geriatric dosages of perphenazine preparations have not been established, but initiation of lower dosages is recommended. Optimal clinical effect or benefit may require lower doses for a longer duration. Dosing of perphenazine may occur before bedtime, if required.

OVERDOSAGE

In the event of overdosage, emergency treatment should be started immediately. Consultation with a poison center should be considered. All patients suspected of having taken an overdose should be hospitalized as soon as possible.
Manifestations
The toxic effects of perphenazine are typically mild to moderate with death occurring in cases involving a large overdose. Overdosage of perphenazine primarily involves the extrapyramidal mechanism and produces the same side effects described under ADVERSE REACTIONS, but to a more marked degree. It is usually evidenced by stupor or coma; children may have convulsive seizures. Signs of arousal may not occur for 48 hours. The primary effects of medical concern are cardiac in origin including tachycardia, prolongation of the QRS or QTcintervals, atrioventricular block, torsade de pointes, ventricular dysrhythmia, hypotension or cardiac arrest, which indicate serious poisoning. Deaths by deliberate or accidental overdosage have occurred with this class of drugs.
Treatment
Treatment is symptomatic and supportive. Induction of emesis is not recommended because of the possibility of a seizure, CNS depression, or dystonic reaction of the head or neck and subsequent aspiration. Gastric lavage (after intubation, if the patient is unconscious) and administration of activated charcoal together with a laxative should be considered. There is no specific antidote.
Standard measures (oxygen, intravenous fluids, corticosteroids) should be used to manage circulatory shock or metabolic acidosis. An open airway and adequate fluid intake should be maintained. Body temperature should be regulated. Hypothermia is expected, but severe hyperthermia may occur and must be treated vigorously. (See CONTRAINDICATIONS.)
An electrocardiogram should be taken and close monitoring of cardiac function instituted if there is any sign of abnormality. Close monitoring of cardiac function is advisable for not less than five days. Vasopressors such as norepinephrine may be used to treat hypotension, but epinephrine should NOT be used.
Hemodialysis and peritoneal dialysis is of no value because of low plasma concentrations of the drug.
Since overdosage is often deliberate, patients may attempt suicide by other means during the recovery phase.

HOW SUPPLIED

Perphenazine tablets, USP are circular, unscored, film-coated white tablets available as:

16 mg: White to off-white, circular, biconvex, film coated tablets debossed with "I 39" on one side and plain on the other side.

NDC: 70518-4484-00

NDC: 70518-4484-01

NDC: 70518-4484-01

PACKAGING: 100 in 1 BOX

PACKAGING: 1 in 1 POUCH

PACKAGING: 30 in 1 BLISTER PACK

Store at 20° to 25°C (68° to 77°F); excursions permitted to 15° to 30°C (59° to 86°F) [See USP Controlled Room Temperature]. Dispense in a tight, light-resistant container.

Repackaged and Distributed By:

Remedy Repack, Inc.

625 Kolter Dr. Suite #4 Indiana, PA 1-724-465-8762

PACKAGE LABEL

DRUG: Perphenazine

GENERIC: Perphenazine

DOSAGE: TABLET

ADMINSTRATION: ORAL

NDC: 70518-4484-0

NDC: 70518-4484-1

NDC: 70518-4484-2

COLOR: white

SHAPE: ROUND

SCORE: No score

SIZE: 11 mm

IMPRINT: I39

PACKAGING: 1 in 1 POUCH

OUTER PACKAGING: 100 in 1 BOX

PACKAGING: 30 in 1 BLISTER PACK

ACTIVE INGREDIENT(S):

- PERPHENAZINE 16mg in 1

INACTIVE INGREDIENT(S):

- CELLULOSE, MICROCRYSTALLINE
- LACTOSE MONOHYDRATE
- SODIUM STARCH GLYCOLATE TYPE A POTATO
- HYDROXYPROPYL CELLULOSE
- MAGNESIUM STEARATE
- POLYETHYLENE GLYCOL 400
- POLYSORBATE 80
- TITANIUM DIOXIDE
- HYPROMELLOSES